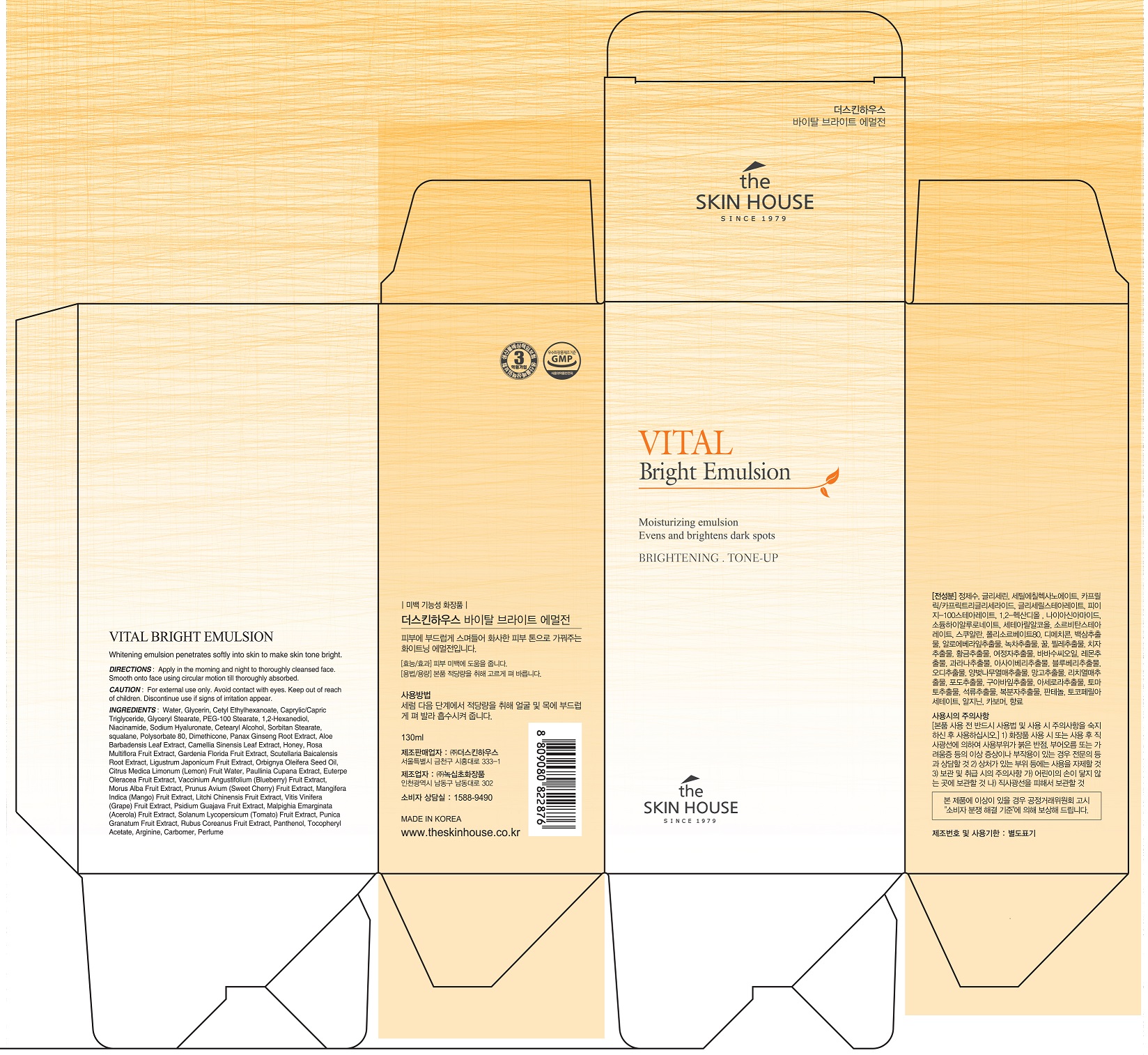 DRUG LABEL: THE SKIN HOUSE Vital BrightEmulsion
NDC: 73590-0050 | Form: EMULSION
Manufacturer: NOKSIBCHO cosmetic Co., Ltd.
Category: otc | Type: HUMAN OTC DRUG LABEL
Date: 20200408

ACTIVE INGREDIENTS: NIACINAMIDE 1 g/100 mL
INACTIVE INGREDIENTS: WATER

Drug Facts

ACTIVE INGREDIENT

Niacinamide

INACTIVE INGREDIENT

Water
Glycerin
Cetyl Ethylhexanoate
Caprylic/Capric Triglyceride
Glyceryl Stearate
PEG-100 Stearate
1,2-Hexanediol
Sodium Hyaluronate
Cetearyl Alcohol
Sorbitan Stearate
Squalane
Polysorbate 80
Dimethicone
Panax Ginseng Root Extract
Aloe Barbadensis Leaf Extract
Camellia Sinensis Leaf Extract
Honey
Rosa Multiflora Fruit Extract
Gardenia Florida Fruit Extract
Scutellaria Baicalensis Root Extract
Orbignya Oleifera Seed Oil
Citrus Medica Limonum (Lemon) Fruit Water
Paullinia Cupana Extract
Euterpe Oleracea Fruit Extract
Vaccinium Angustifolium (Blueberry) Fruit Extract
Morus Alba Fruit Extract
Prunus Avium (Sweet Cherry) Fruit Extract
Mangifera Indica (Mango) Fruit Extract
Litchi Chinensis Fruit Extract
Vitis Vinifera (Grape) Fruit Extract
Psidium Guajava Fruit Extract
Malpighia Emarginata (Acerola) Fruit Extract
Solanum Lycopersicum (Tomato) Fruit Extract
Punica Granatum Fruit Extract
Rubus Coreanus Fruit Extract
Panthenol
Tocopheryl Acetate
Arginine
Carbomer
Parfum

PURPOSE

skin brightening

keep out of reach of the children

INDICATIONS AND USAGE

apply proper amount to the skin

WARNINGS

For external use only
When using this product

■ if the following symptoms occurs after use, stop use and consult with a skin specialist

red specks, swelling, itching

■ don’t use on the part where there is injury, eczema, or dermatitis

Keep out of reach of children

■ if swallowed, get medical help or contact a person control center immediately